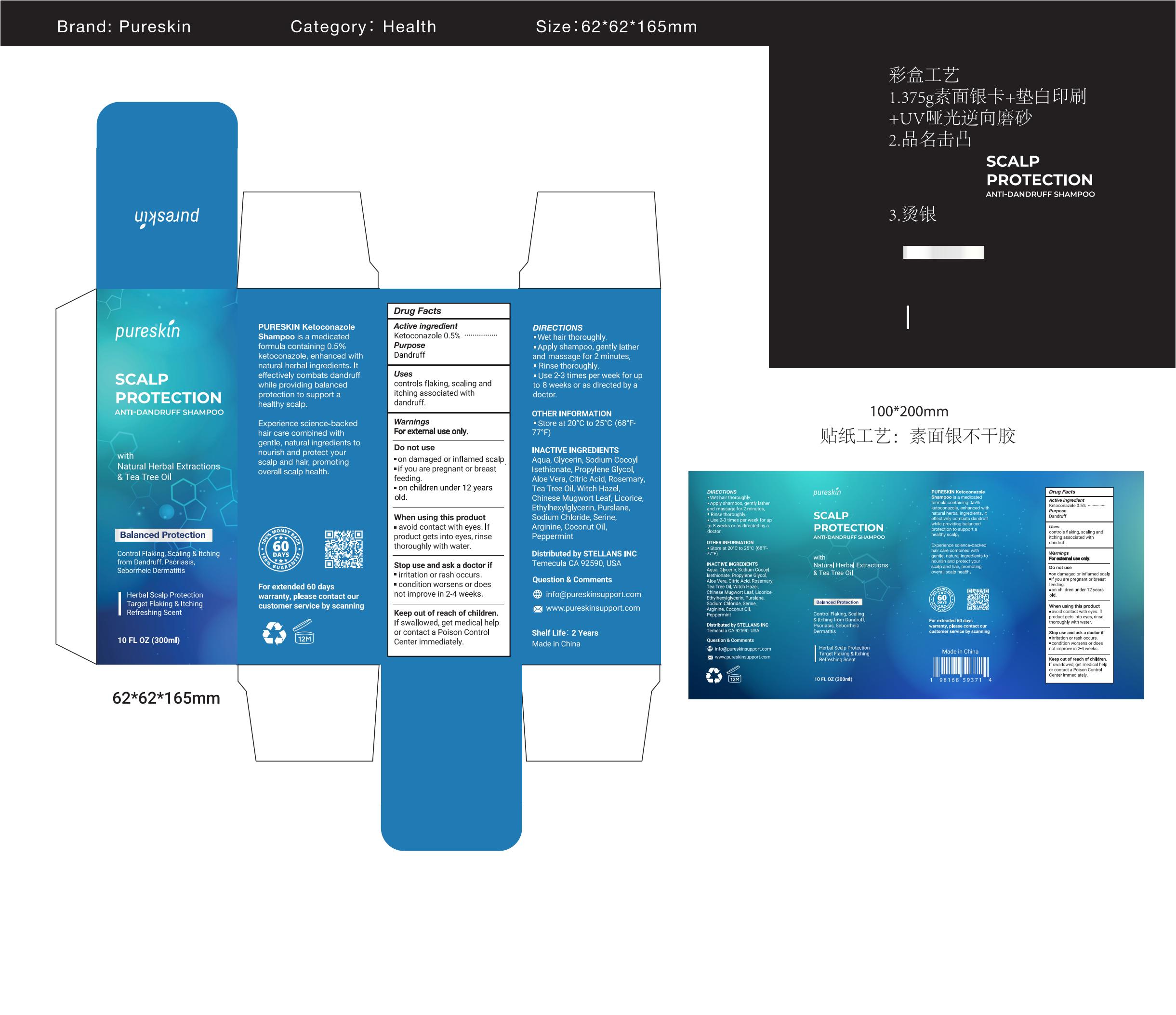 DRUG LABEL: Pureskin Scalp Protection anti dandruff shampoo.
NDC: 83887-004 | Form: SHAMPOO
Manufacturer: Changsha Beiliang E-commerce Co., Ltd
Category: otc | Type: HUMAN OTC DRUG LABEL
Date: 20250203

ACTIVE INGREDIENTS: KETOCONAZOLE 0.5 g/100 mL
INACTIVE INGREDIENTS: GLYCERIN; PROPYLENE GLYCOL; PEPPERMINT; SERINE; SODIUM COCOYL ISETHIONATE; ALOE VERA LEAF; COCONUT OIL; CITRIC ACID; TEA TREE OIL; WITCH HAZEL; ARTEMISIA ARGYI LEAF; LICORICE; ARGININE; AQUA; ROSEMARY; PURSLANE; SODIUM CHLORIDE; ETHYLHEXYLGLYCERIN

83887-004

Active Ingredient

ketoconazole 0.5%

Purpose

dandruff

Use

controls flaking, scaling and itching associated with dandruff.

Warnings

For external use only.

Do not use

on damaged or inflamed scalp.
if you are pregnant or breast feeding.
on children under 12 years old.

When Using

avoid contact with eyes. If product gets into eyes, rinse thoroughly with water.
Keep out of the reach of young children.

Stop Use

No improvement after 4 weeks of normal usage.

Ask Doctor

irritation or rash occurs.
condition worsens or does not improve in 2-4 weeks.

Keep Out Of Reach Of Children

If swallowed, get medical help or contact a Poison Control Center immediately.

Directions

Wet hair thoroughly.
Apply shampoo, gently lather and massage for 2 minutes, Rinse thoroughly.
Use 2-3 times per week for up to 8 weeks or as directed by a doctor

Other information

Store at 20°C to 25°C (68°F - 77°F)

Inactive ingredients

Aqua
Glycerin
Sodium Cocoyl Isethionate
Propylene Glycol
Aloe Vera
Citric Acid
Rosemary
Tea Tree Oil
Witch Hazel
Chinese Mugwort Leaf
Licorice
Ethylhexylglycerin
Purslane
Sodium Chloride
Serine
Arginine
Coconut Oil
Peppermint

Questions

info@pureskinsupport.com
www.pureskinsupport.com